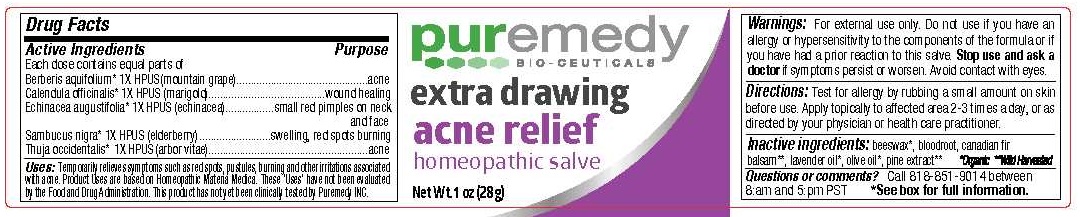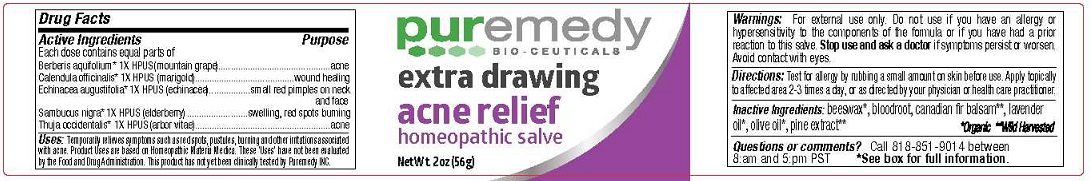 DRUG LABEL: EXTRA DRAWING ACNE RELIEF
NDC: 52810-103 | Form: SALVE
Manufacturer: PUREMEDY
Category: homeopathic | Type: HUMAN OTC DRUG LABEL
Date: 20240111

ACTIVE INGREDIENTS: MAHONIA AQUIFOLIUM FRUITING TOP 1 [hp_X]/100 g; CALENDULA OFFICINALIS FLOWER 1 [hp_X]/100 g; ECHINACEA ANGUSTIFOLIA 1 [hp_X]/100 g; SAMBUCUS NIGRA FLOWER 1 [hp_X]/100 g; THUJA OCCIDENTALIS LEAF 1 [hp_X]/100 g
INACTIVE INGREDIENTS: YELLOW WAX; SANGUINARIA CANADENSIS ROOT; CANADA BALSAM; LAVENDER OIL; OLIVE OIL; PINUS MUGO SUBSP. MUGO LEAFY TWIG

ACNE RELIEF - EXTRA DRAWING (52810-103)

ACTIVE INGREDIENTS

ORGANIC BERBERIS AQUIFOLIUM (1X) HPUS (MOUNTAIN GRAPE)

ORGANIC CALENDULA OFFICINALIS (1X) HPUS (MARIGOLD)

ORGANIC ECHINACEA ANGUSTIFOLIA (1X) HPUS (ECHINACEA)

ORGANIC SAMBUCUS NIGRA (1X) HPUS (ELDERBERRY)

ORGANIC THUJA OCCIDENTALIS (1X) HPUS (ARBOR VITAE)

PURPOSE

ACNE

WOUND HEALING

SMALL RED PIMPLES ON NECK AND FACE

SWELLING, RED SPOTS BURNING

ACNE

USES

TEMPORARILY RELIEVES SYMPTOMS SUCH AS RED SPOTS, PUSTULES, BURNING AND OTHER IRRITATIONS ASSOCIATED WITH ACNE. PRODUCT USES ARE BASED ON HOMEOPATHIC MATERIA MEDICA. THESE 'USES' HAVE NOT BEEN EVALUATED BY THE FOOD AND DRUG ADMINISTRATION. THIS PRODUCT HAS NOT YET BEEN CLINICALLY TESTED BY PUREMEDY INC.

DIRECTIONS

TEST FOR ALLERGY BY RUBBING A SMALL AMOUNT ON SKIN BEFORE USE. APPLY TOPICALLY TO AFFECTED AREA 2-3 TIMES A DAY, OR AS DIRECTED BY YOUR PHYSICIAN OR HEALTH CARE PRACTITIONER.

INACTIVE INGREDIENTS

BEESWAX*, BLOODROOT, CANADIAN FIR BALSAM**, LAVENDER OIL*, OLIVE OIL*, PINE EXTRACT**

*ORGANIC **WILD HARVESTED

WARNINGS

FOR EXTERNAL USE ONLY. DO NOT USE IF YOU HAVE AN ALLERGY OR HYPERSENSITIVITY TO THE COMPONENTS OF THE FORMULA OR IF YOU HAVE HAD A PRIOR REACTION TO THIS SALVE. STOP USE AND ASK A DOCTOR IF SYMPTOMS PERSIST OR WORSEN. AVOID CONTACT WITH EYES.

KEEP OUT OF REACH OF CHILDREN.

IF SWALLOWED CONTACT A HEALTH CARE PROVIDER OR POISON CONTROL CENTER RIGHT AWAY.

QUESTIONS OR COMMENTS?

CALL 818-851-9014 BETWEEN 8:AM AND 5:PM PST

*SEE BOX FOR FULL INFORMATION.